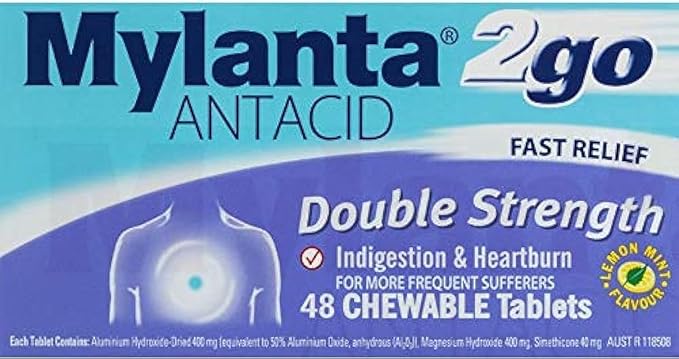 DRUG LABEL: MYLANTA 2go ANTACID DOUBLE STRENGTH
NDC: 84177-0801 | Form: TABLET, CHEWABLE
Manufacturer: MEDIA NETWORKS SYDNEY PTY LIMITED
Category: otc | Type: HUMAN OTC DRUG LABEL
Date: 20240319

ACTIVE INGREDIENTS: DIMETHICONOL (40 CST) 40 mg/1 g; ALUMINUM HYDROXIDE 400 mg/1 g
INACTIVE INGREDIENTS: DIMETHICONE 1000; MAGNESIUM HYDROXIDE 400 mg/1 g; SILICON DIOXIDE; SPEARMINT OIL; SUCROSE; MAGNESIUM STEARATE; STARCH, CORN; MANNITOL; WATER

DOSAGE AND ADMINISTRATION

Dosage Form Tablet, chewable Route of Administration Oral Visual Identification A white, round, bevelled edged tablet, plain on one side and embossed with "WL 478" on the other

Warnings No Warnings included on Record

INACTIVE INGREDIENT

Other Ingredients (Excipients) dimeticone 1000 dimeticonol Flavour magnesium stearate maize starch mannitol purified water silicon dioxide Spearmint oil sucrose

Permitted Indications No Permitted Indications included on Record

Keep out of Reach of Children Section

PURPOSE

Specific Indications Fast relief from upset stomach, flatulence, wind pain, gastric hyperacidity, indigestion, heartburn and oesophageal reflux.

ACTIVE INGREDIENT

aluminium hydroxide 400 mg magnesium hydroxide 400 mg simethicone 40 mg

PACKAGE LABEL

Mylanta 2go Double Strength Chewable Antacid Tablets 48 Pack